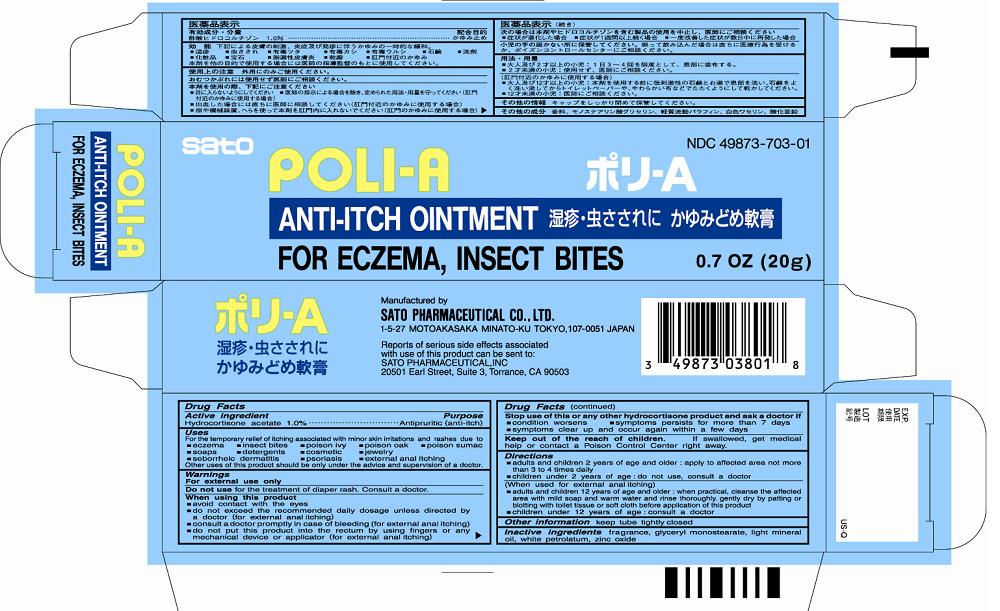 DRUG LABEL: Poli-A
NDC: 49873-703 | Form: OINTMENT
Manufacturer: Sato Pharmaceutical Co., Ltd.
Category: otc | Type: HUMAN OTC DRUG LABEL
Date: 20231128

ACTIVE INGREDIENTS: HYDROCORTISONE ACETATE 1 g/100 g
INACTIVE INGREDIENTS: LIGHT MINERAL OIL; GLYCERYL MONOSTEARATE; PETROLATUM; ZINC OXIDE

Poli-A

Uses
For the temporary relief of itching associated with minor skin irritations and rashes due to
■eczema ■insect bites ■poison ivy ■poison oak ■poison sumac
■soaps ■detergents ■cosmetic ■jewelry
■seborrheic determatis ■psoriasis ■external anal itching
Other uses of this product should be only under the advice and supervision of a doctor.

Warnings
For external use only

Do not use for the treatment of diaper rash. Consult a doctor.

When using this product
■avoid contact with the eyes
■do not exceed the recommended daily dosage unless directed by a doctor (for external anal itching)
■consult a doctor promptly in case of bleeding (for external anal itching)
■do not put this product into the rectum by using fingers or any mechanical device or applicator (for external anal itching)

Stop use of this or any other hydrocortisone product and ask a doctor if
■condition worsens ■symptoms persist for more than 7 days.
■symptoms clear up and occur again within a few days.

Keep out of reach of children. If swallowed, get medical help or contact a Poison Control Center right away.

Directions
■adults and children 2 years of age and older: apply to affected area not more than 3 to 4 times daily.
■children under 2 years of age: do not use, consult a doctor
(When used for external anal itching)
■adults and children 12 years of age and older: when practical, cleanse the affected area with mild soap and warm water and rinse thoroughly. gently dry by patting or blotting with toilet tissue or soft cloth before application of this product
■children under 12 years of age: consult a doctor

Other information keep tube tightly closed

INACTIVE INGREDIENT

Inactive ingredients fragrance, glyceryl monostearate, light mineral oil, white petrolatum, zinc oxide

Active ingredient
Hydrocortisone acetate 1.0%

Purpose Antipruritic (anti-itch)